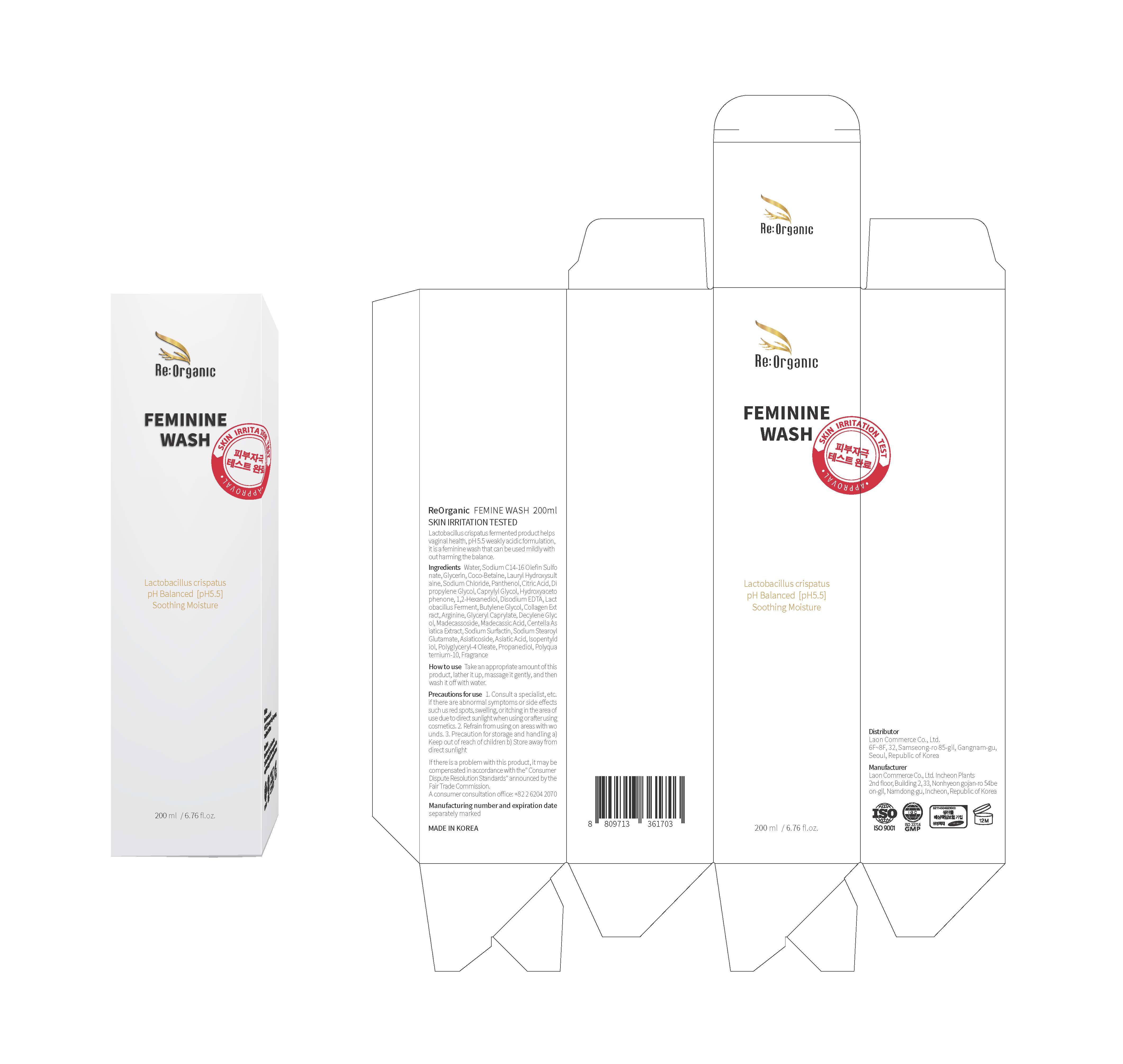 DRUG LABEL: Reorganic Feminine wash
NDC: 82083-0021 | Form: GEL
Manufacturer: LAON COMMERCE co ltd
Category: otc | Type: HUMAN OTC DRUG LABEL
Date: 20230704

ACTIVE INGREDIENTS: LACTOBACILLUS CRISPATUS 0.1 g/100 mL
INACTIVE INGREDIENTS: PANTHENOL; GLYCERIN; WATER; CENTELLA ASIATICA

ACTIVE INGREDIENT

Lactobacillus crispatus

INACTIVE INGREDIENT

Water
Sodium C14-16 Olefin Sulfonate
Glycerin
Coco-Betaine
Lauryl Hydroxysultaine
Sodium Chloride
Panthenol
Citric Acid
Dipropylene Glycol
Caprylyl Glycol
Hydroxyacetophenone
1,2-Hexanediol
Disodium EDTA
Lactobacillus Ferment
Butylene Glycol
Collagen Extract
Arginine
Glyceryl Caprylate
Decylene Glycol
Madecassoside
Madecassic Acid
Centella Asiatica Extract
Sodium Surfactin
Sodium Stearoyl Glutamate
Asiaticoside
Asiatic Acid
Isopentyldiol
Polyglyceryl-4 Oleate
Propanediol
Polyquaternium-10
Fragrance

PURPOSE

skin protect

KEEP OUT OF REACH OF THE CHILDREN

INDICATIONS AND USAGE

Take an appropriate amount of this product, lather it up, massage it gently, and then wash it off with water

WARNINGS

Precautions for use 1. Consult a specialist, etc. if there are abnormal symptoms or side effects such us red spots, swelling, or itching in the area of use due to direct sunlight when using or after using cosmetics. 2. Refrain from using on areas with wo unds. 3. Precaution for storage and handling a) Keep outof reach of children b) Store away from direct sunlight

DOSAGE AND ADMINISTRATION

topical use only